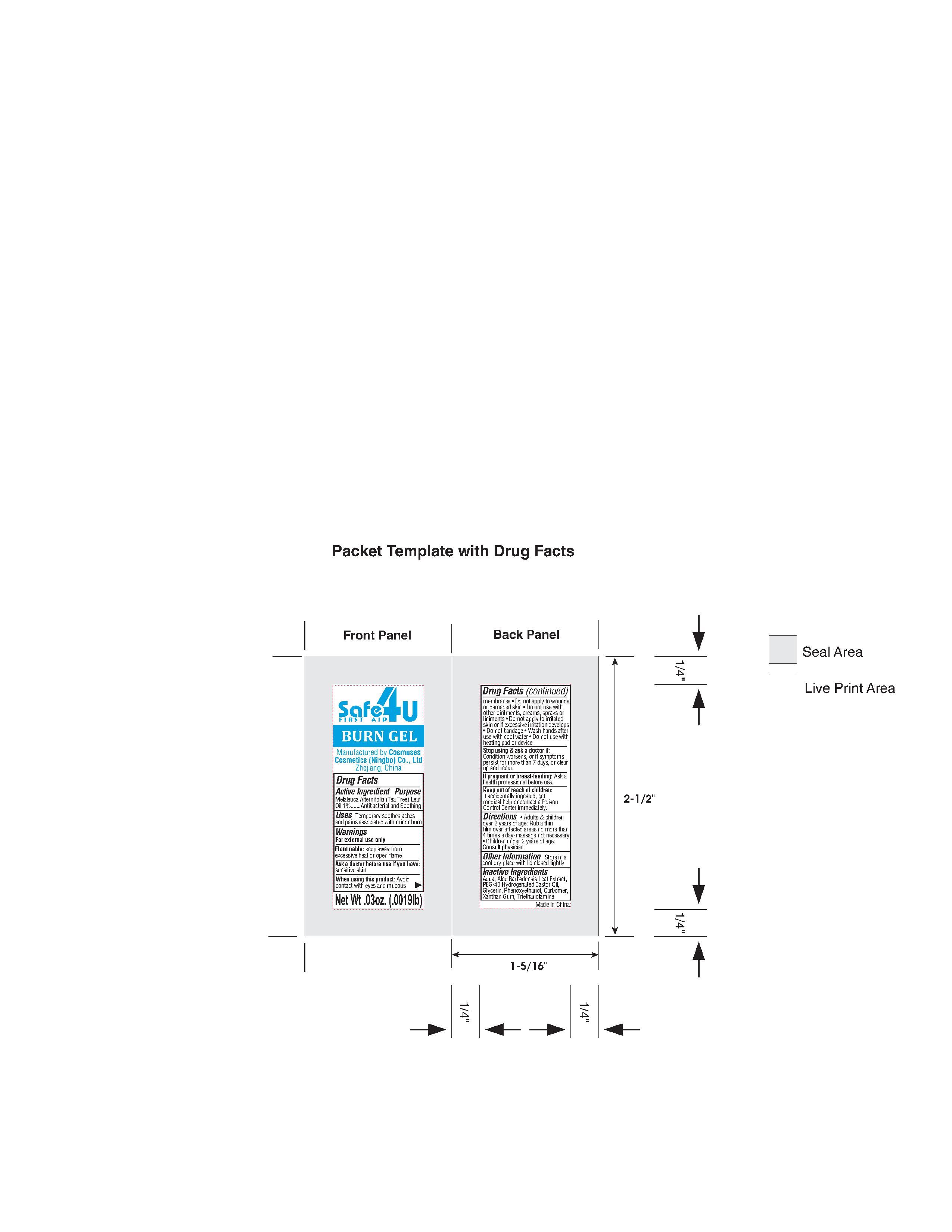 DRUG LABEL: burn gel
NDC: 82953-045 | Form: GEL
Manufacturer: Cosmuses Cosmetics (Ningbo) Co., Ltd.
Category: otc | Type: HUMAN OTC DRUG LABEL
Date: 20250406

ACTIVE INGREDIENTS: MELALEUCA ALTERNIFOLIA (TEA TREE) LEAF OIL 1 g/100 g
INACTIVE INGREDIENTS: PHENOXYETHANOL; GLYCERIN; CARBOMER 940; ALOE BARBADENSIS LEAF; WATER; XANTHAN GUM; PEG-40 HYDROGENATED CASTOR OIL; TRIETHANOLAMINE

burn gel

Drug Facts

Active ingredients

melaleuca alternifolia (tea tree) leaf oil 1%

Purpose

antibacterial and soothing

Uses

Temporary soothes aches and pains associated with minor burn

warnings

For external use only.

ENVIRONMENTAL WARNING

Flammable: keep away from excessice heat or open flame.

Ask a doctor before use if you have: sensitive skin

When using this product: Avoid contact with eyes and mucous membranes.

Do no apply to wounds or damaged skin.

Do not use with other ointments, creams, sprays or liniments.

Do not apply to irritated skin or if excessive irritation develops.

Do not bandage.

Wash hands after use with cool water.

Do not use with heating pad or device.

Stop use and ask a doctor if:

Condition worsens, or if symptoms persist for more than 7 days, or clear up and recur.

PREGNANCY OR BREAST FEEDING

If pregnant or breast-feeding: ask a health professional before use.

Keep out of reach of children. If accidentally ingested, get medical help or contact a Poison Control Center immediately.

Directions

- Adults & children over 2 years of age: rub a thnk film over affected areas no more than 4 times a day- massage not necessary
- Children under 2 years of age: consult physician.

other information

Store in a cool dry place with lid closed tightly.

Inactive ingredients

Aqua, Aloe Barbadensis Leaf Extract, PEG-40 Hydrogenated Castor Oil, Glycerin, Phenoxyethanol, Carbomer, Xanthan Gum, Triethanolamine.